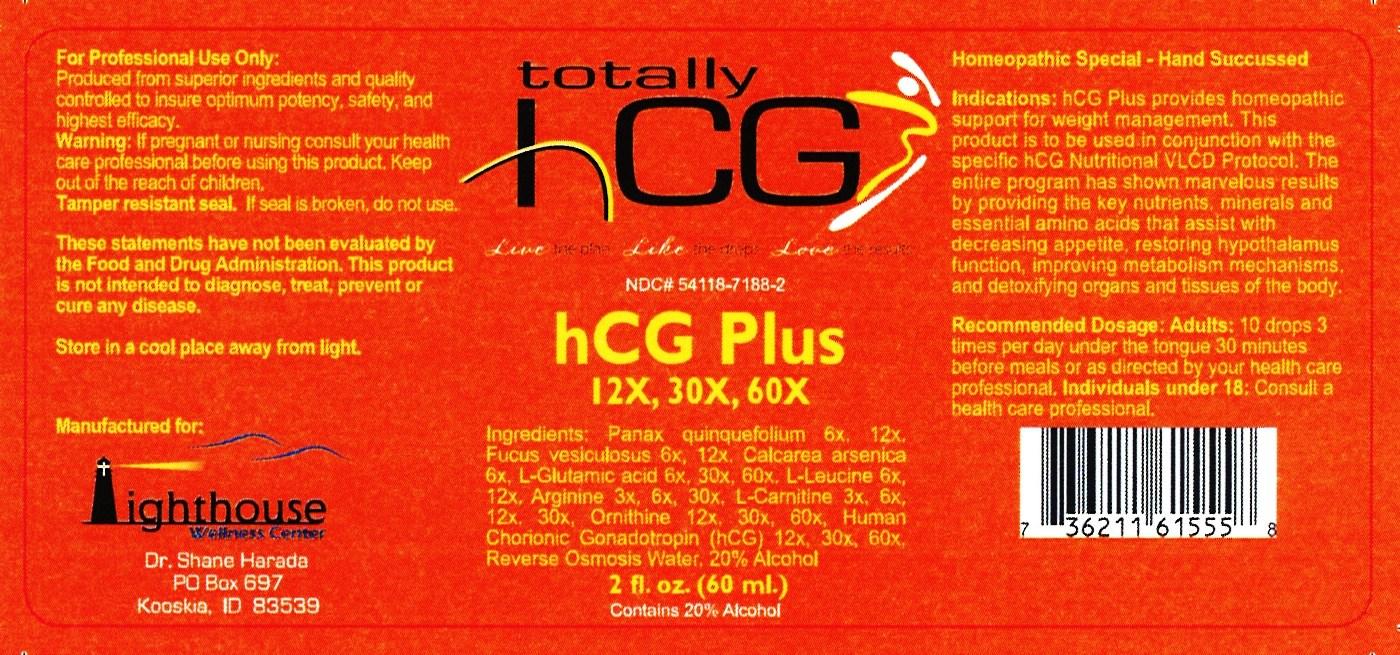 DRUG LABEL: HCG Plus
NDC: 54118-7188 | Form: SOLUTION/ DROPS
Manufacturer: ABCO Laboratories, Inc.
Category: homeopathic | Type: HUMAN OTC DRUG LABEL
Date: 20140516

ACTIVE INGREDIENTS: AMERICAN GINSENG 6 [hp_X]/60 mL; FUCUS VESICULOSUS 6 [hp_X]/60 mL; CALCIUM ARSENATE 6 [hp_X]/60 mL; GLUTAMIC ACID 6 [hp_X]/60 mL; LEUCINE  6 [hp_X]/60 mL; ARGININE  3 [hp_X]/60 mL; ACETYLCARNITINE 3 [hp_X]/60 mL; ORNITHINE 12 [hp_X]/60 mL; GONADOTROPHIN, CHORIONIC 12 [hp_X]/60 mL
INACTIVE INGREDIENTS: WATER; ALCOHOL

HCG Plus

ACTIVE INGREDIENT

- Panax Quinquefolium 6x, 12x
- Fucus Vesiculosus 6x, 12x
- Calcarea Arsenica 6x
- L-Glutamic Acid 6x, 30x, 60x
- L-Leucine 6x, 12x
- Arginine 3x, 6x, 30x
- Acetyl L-Carnitine 3x, 6x, 12x, 30x
- Ornithine 12x, 30x, 60x
- Human Chorionic Gonadotropin (hCG) 12x, 30x, 60x

PURPOSE

- hCG Plus provides homeopathic support for weight management. This product is to be used in conjunction with the specific hCG Nutritional VLCD protocol.
- The entire program has shown marvelous results by providing the key nutrients, minerals and essential amino acids that assist with decreasing appetite, restoring hypothalamus function, improving metabolism mechanisms, and detoxifying organs and tissues of the body.

- Keep out of reach of children

INDICATIONS AND USAGE

- hCG Plus provides homeopathic support for weight management. This product is to be used in conjunction with the specific hCG Nutritional VLCD protocol.
- The entire program has shown marvelous results by providing the key nutrients, minerals and essential amino acids that assist with decreasing appetite, restoring hypothalamus function, improving metabolism mechanisms, and detoxifying organs and tissues of the body.

- Keep out of reach of children.
- If pregnant or nursing, consult a health professional before using this product
- Tamper seal: If seal is broken do not use.

DOSAGE AND ADMINISTRATION

- 10 drops under the tongue, 3 times per day or as directed by a health professional.
- Use 30 min. before meals.
- Consult a physician for use in children under 12 years of age.

INACTIVE INGREDIENT

- Reversed Osmosis Water
- 20% alcohol

- image of label
- hcgpluslabel.jpg